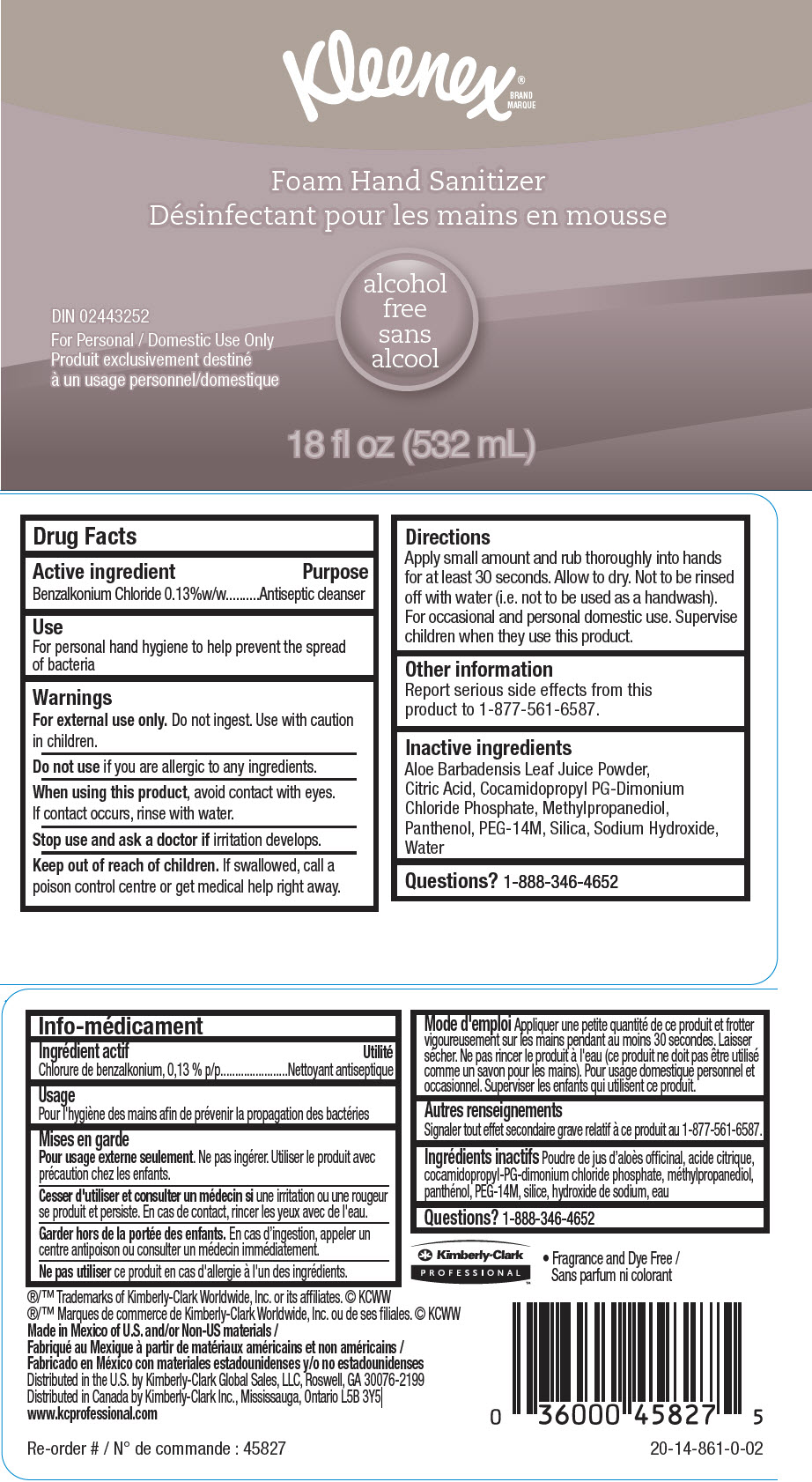 DRUG LABEL: KLEENEX Foam Hand Sanitizer
NDC: 55118-701 | Form: SOLUTION
Manufacturer: Kimberly-Clark
Category: otc | Type: HUMAN OTC DRUG LABEL
Date: 20241210

ACTIVE INGREDIENTS: Benzalkonium Chloride 1.3 mg/1000 mL
INACTIVE INGREDIENTS: Water; Methylpropanediol; Cocamidopropyl Propylene Glycol-Dimonium Chloride Phosphate; Polyethylene Oxide 600000; Citric Acid Monohydrate; Silicon Dioxide; Aloe; Panthenol; Sodium Hydroxide

KLEENEX® Foam Hand Sanitizer

Drug Facts

Active ingredient

Benzalkonium Chloride 0.13%w/w

Purpose

Antiseptic cleanser

Use

For personal hand hygiene to help prevent the spread of bacteria

Warnings

For external use only. Do not ingest. Use with caution in children.

Do not use if you are allergic to any ingredients.

When using this product, avoid contact with eyes.

If contact occurs, rinse with water.

Stop use and ask a doctor if irritation develops.

Keep out of reach of children. If swallowed, call a poison control centre or get medical help right away.

Directions

Apply small amount and rub thoroughly into hands for at least 30 seconds. Allow to dry. Not to be rinsed off with water (i.e. not to be used as a handwash). For occasional and personal domestic use. Supervise children when they use this product.

Other information

Report serious side effects from this product to 1-877-561-6587.

Inactive ingredients

Aloe Barbadensis Leaf Juice Powder, Citric Acid, Cocamidopropyl PG-Dimonium Chloride Phosphate, Methylpropanediol, Panthenol, PEG-14M, Silica, Sodium Hydroxide, Water

Questions?

1-888-346-4652

Distributed in the U.S. by Kimberly-Clark Global Sales, LLC, Roswell, GA 30076-2199
Distributed in Canada by Kimberly-Clark Inc., Mississauga, Ontario L5B 3Y5

PRINCIPAL DISPLAY PANEL - 532 mL Bottle Label

Kleenex®

Foam Hand Sanitizer

alcohol
free

DIN: 02443252

For Personal / Domestic Use Only

18 fl oz (532 mL)